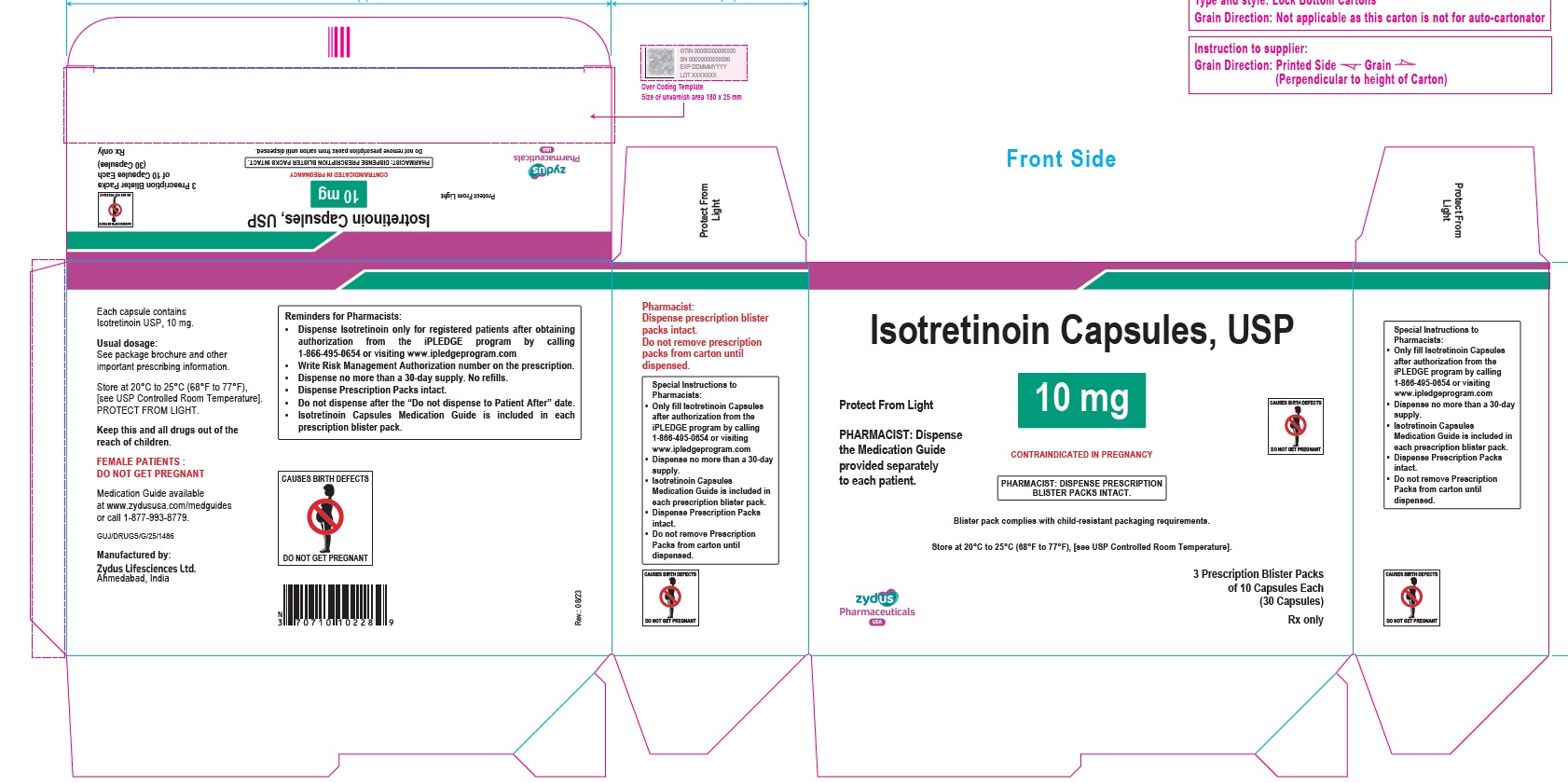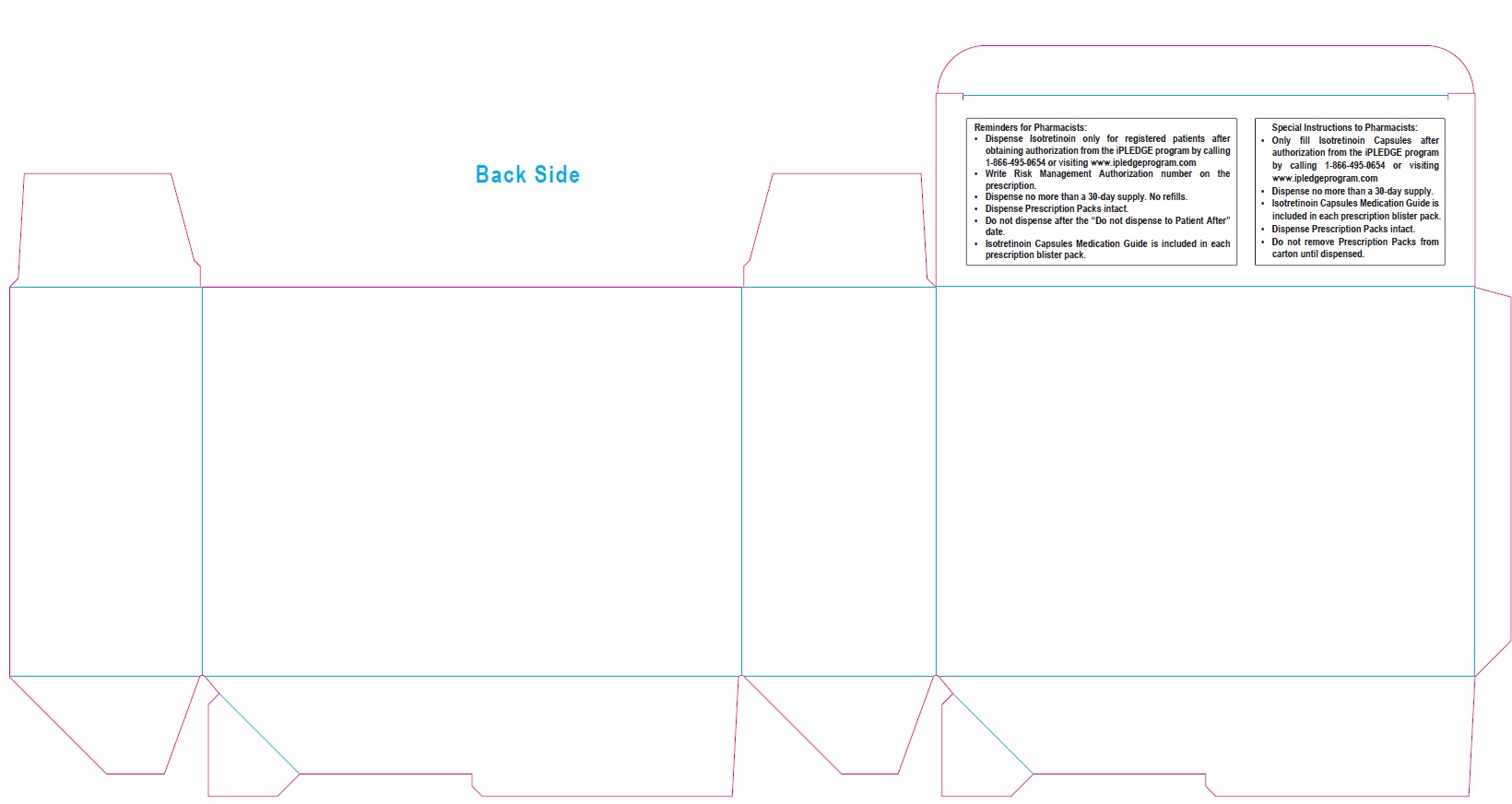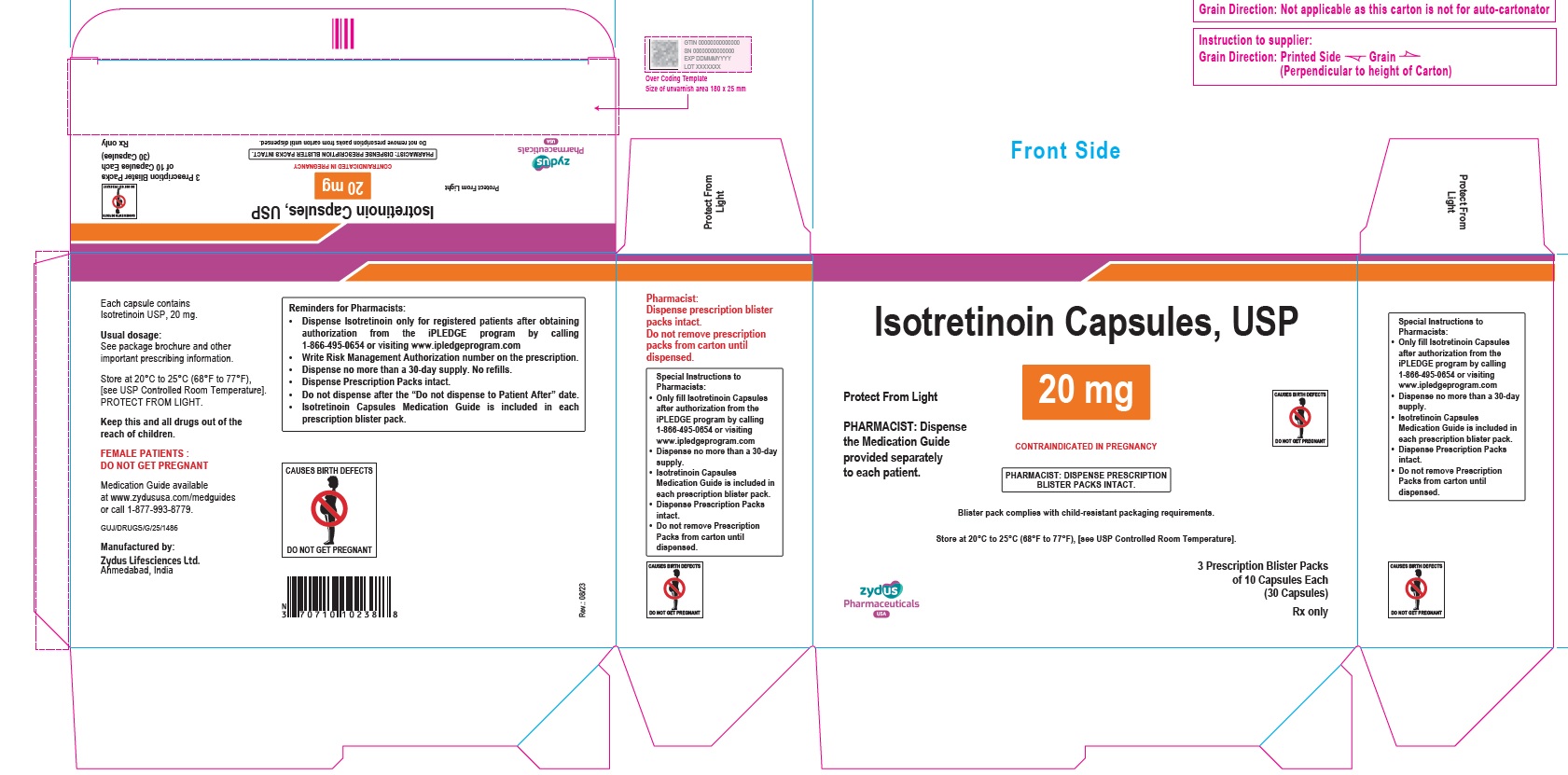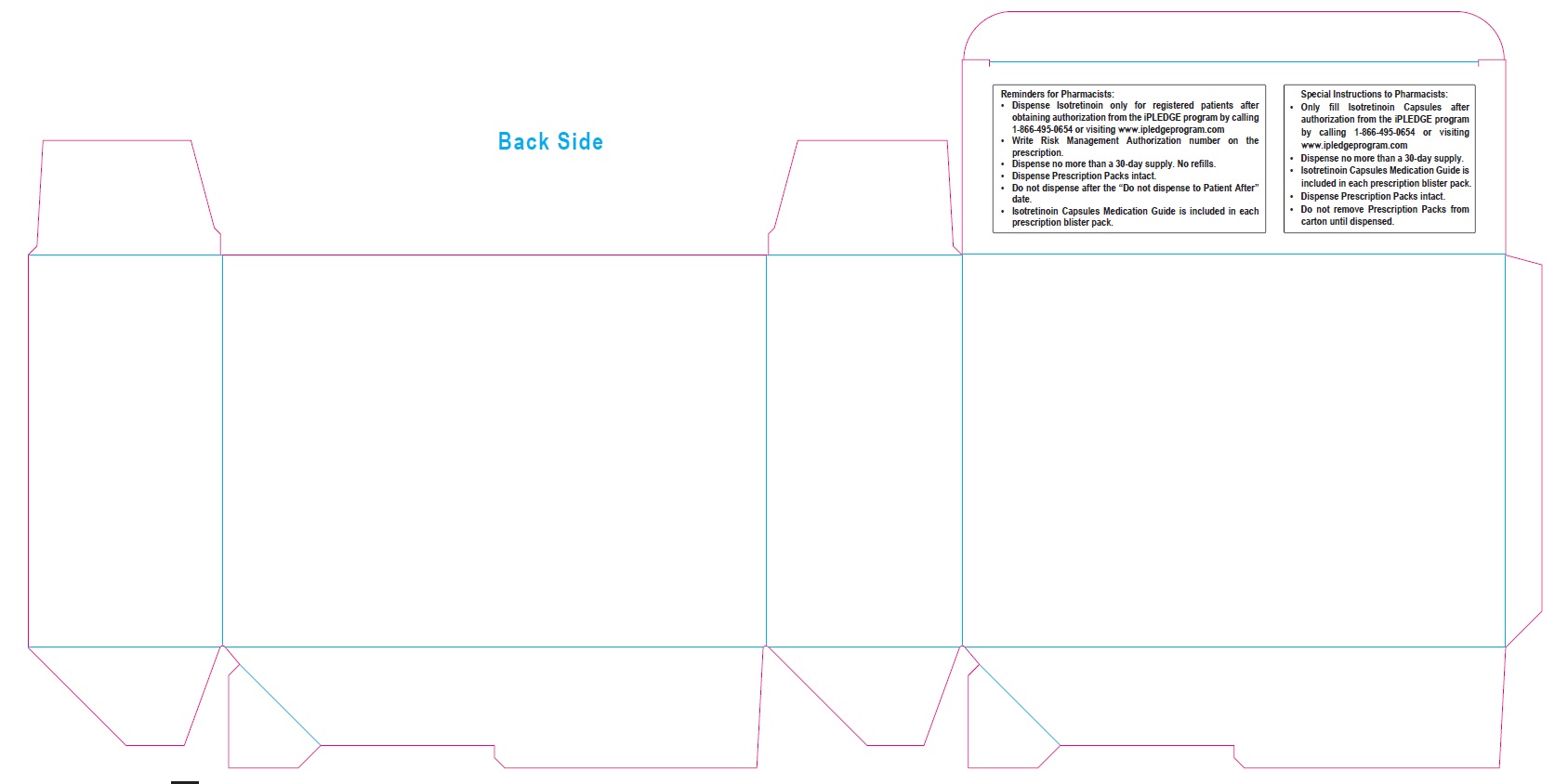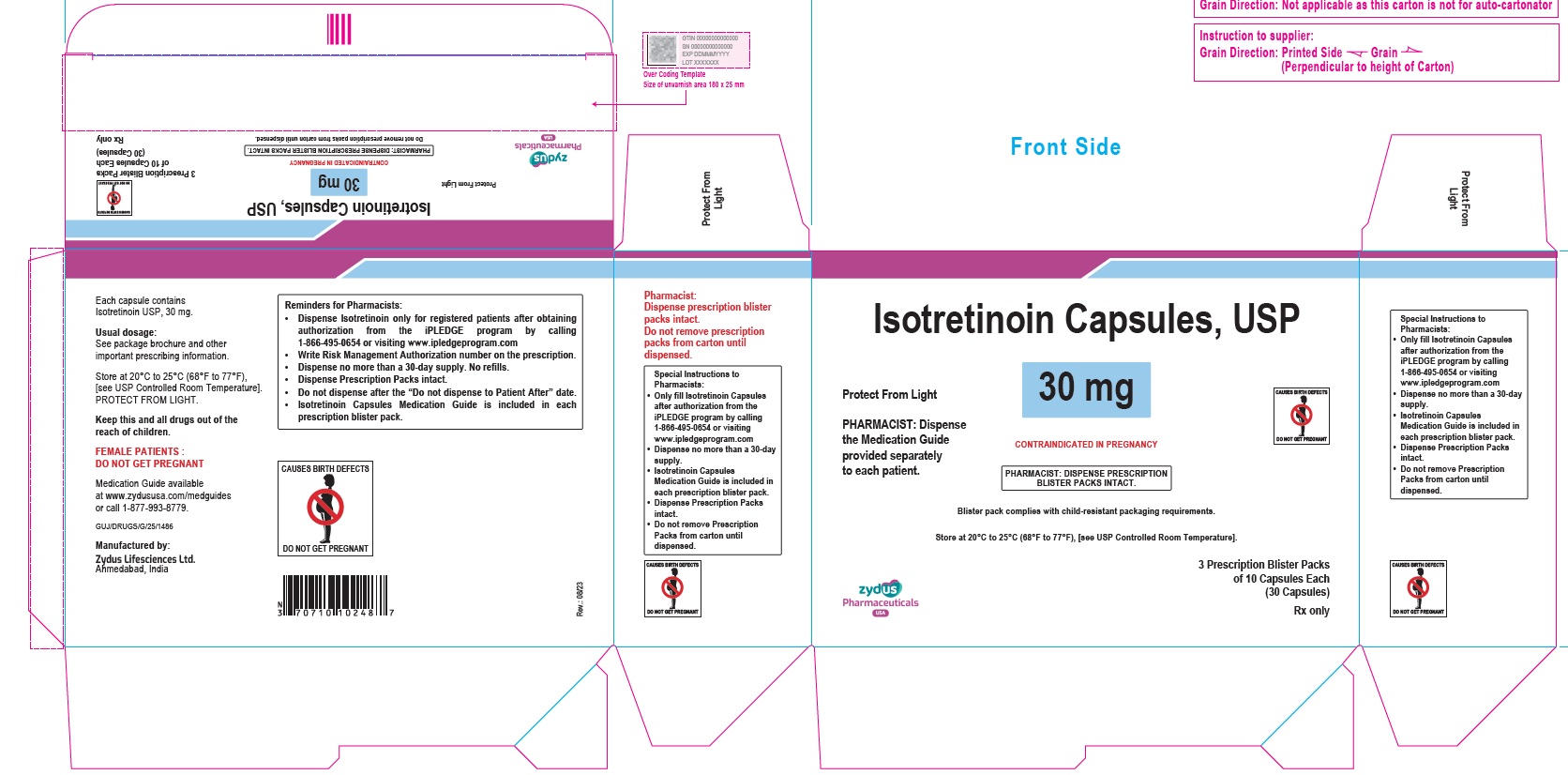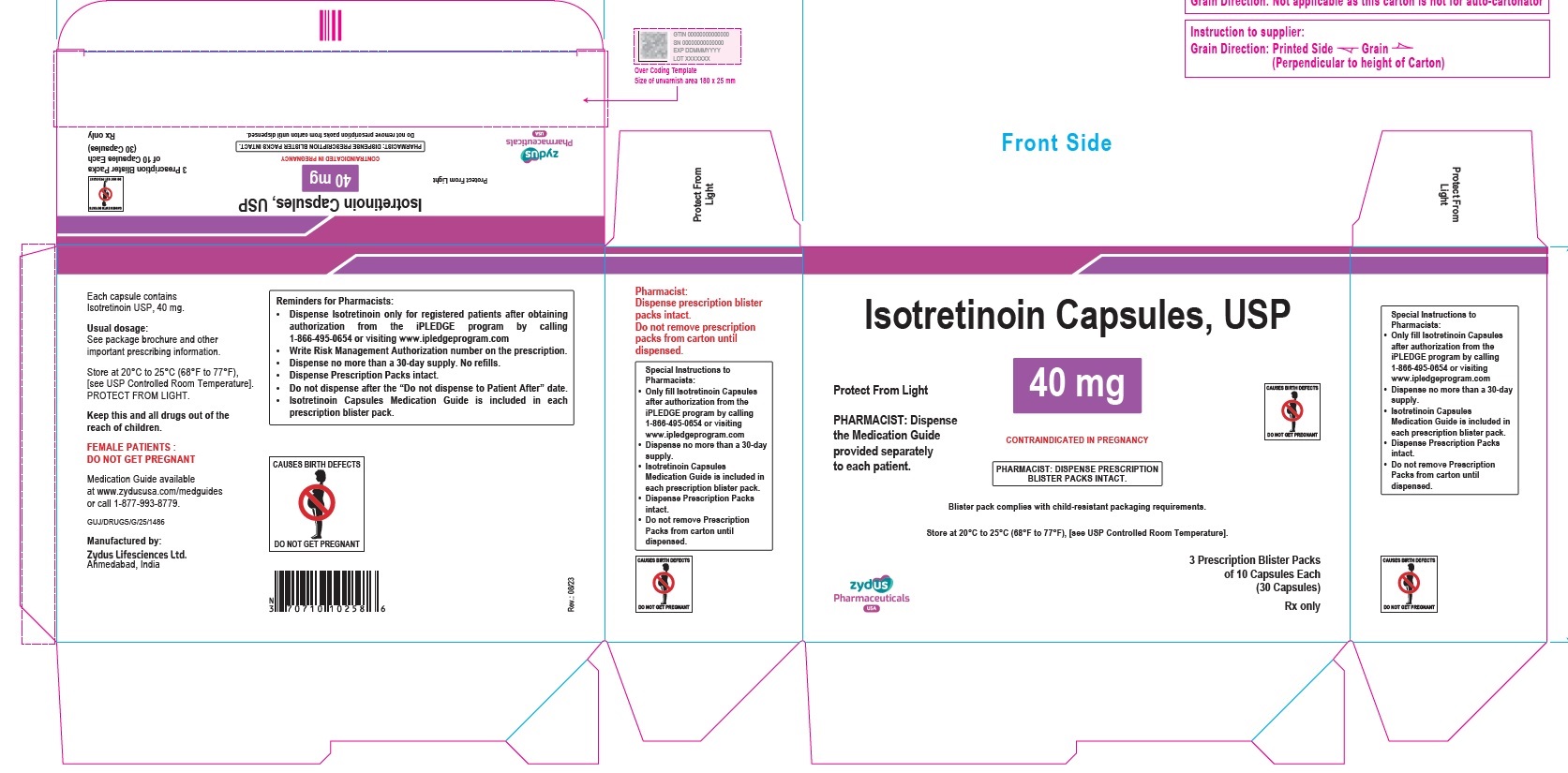 DRUG LABEL: Isotretinoin
NDC: 70771-1557 | Form: CAPSULE
Manufacturer: Zydus Lifesciences Limited
Category: prescription | Type: HUMAN PRESCRIPTION DRUG LABEL
Date: 20241130

ACTIVE INGREDIENTS: ISOTRETINOIN 10 mg/1 1
INACTIVE INGREDIENTS: ALCOHOL; AMMONIA; BUTYLATED HYDROXYANISOLE; EDETATE DISODIUM; FERRIC OXIDE RED; FERRIC OXIDE YELLOW; FERROSOFERRIC OXIDE; GELATIN; GLYCERIN; HYDROGENATED SOYBEAN OIL; ISOPROPYL ALCOHOL; POLYETHYLENE GLYCOL 400; POLYVINYL ACETATE PHTHALATE; PROPYLENE GLYCOL; SOYBEAN OIL; TITANIUM DIOXIDE; WATER; WHITE WAX

Isotretinoin Capsules, USP
Rx Only
CAUSES BIRTH DEFECTS

.

PACKAGE LABEL.PRINCIPAL DISPLAY PANEL

NDC 70771-1557-8

Isotretinoin Capsules, USP 10 mg

30 Capsules

Rx only

NDC 70771-1558-8

Isotretinoin Capsules, USP 20 mg

30 Capsules

Rx only

NDC 70771-1559-8

Isotretinoin Capsules, USP 30 mg

30 Capsules

Rx only

NDC 70771-1560-8

Isotretinoin Capsules, USP 40 mg

30 Capsules

Rx only